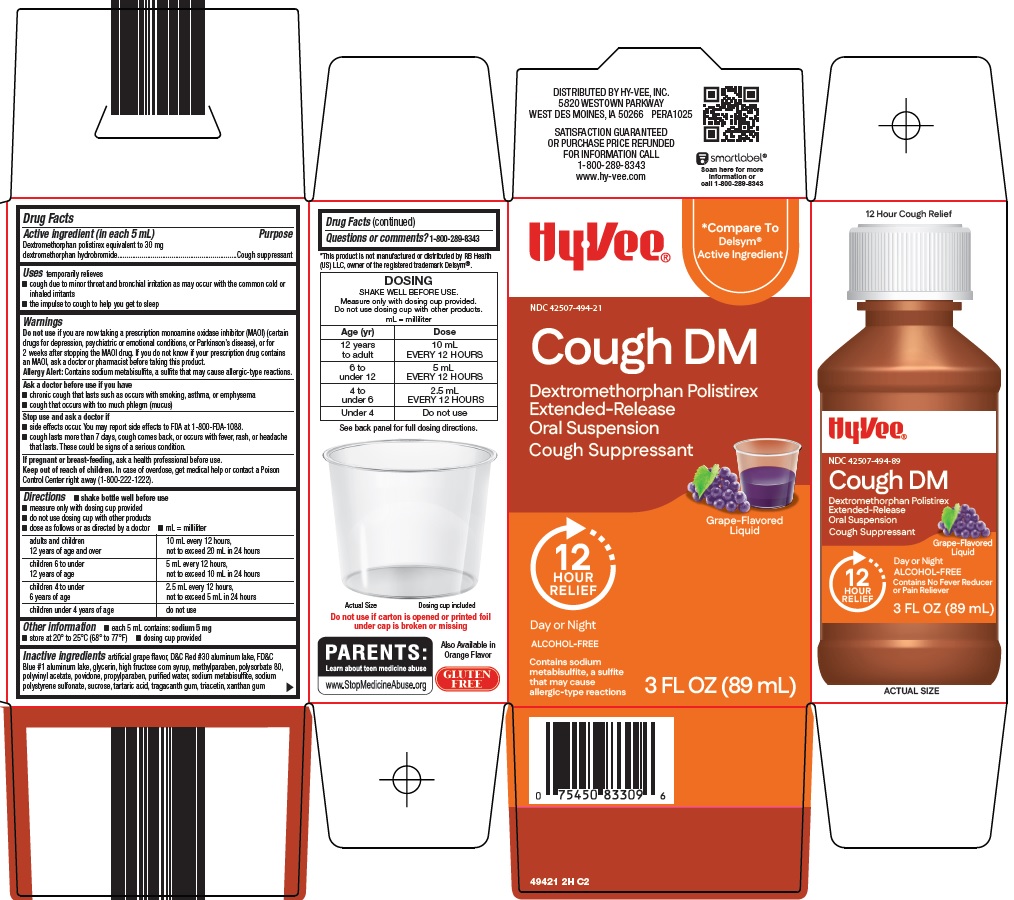 DRUG LABEL: cough dm
NDC: 42507-494 | Form: SUSPENSION, EXTENDED RELEASE
Manufacturer: HyVee Inc
Category: otc | Type: HUMAN OTC DRUG LABEL
Date: 20260127

ACTIVE INGREDIENTS: DEXTROMETHORPHAN HYDROBROMIDE 30 mg/5 mL
INACTIVE INGREDIENTS: D&C RED NO. 30 ALUMINUM LAKE; FD&C BLUE NO. 1 ALUMINUM LAKE; GLYCERIN; HIGH FRUCTOSE CORN SYRUP; METHYLPARABEN; POLYSORBATE 80; POLYVINYL ACETATE; POVIDONE, UNSPECIFIED; PROPYLPARABEN; WATER; SODIUM METABISULFITE; SODIUM POLYSTYRENE SULFONATE; SUCROSE; TARTARIC ACID; TRAGACANTH; TRIACETIN; XANTHAN GUM

Hy-Vee, Inc. Cough DM Drug Facts

Active ingredient (in each 5 mL)

Dextromethorphan polistirex equivalent to 30 mg dextromethorphan hydrobromide

Purpose

Cough suppressant

Uses

temporarily relieves

- cough due to minor throat and bronchial irritation as may occur with the common cold or inhaled irritants
- the impulse to cough to help you get to sleep

Warnings

Do not use

if you are now taking a prescription monoamine oxidase inhibitor (MAOI) (certain drugs for depression, psychiatric or emotional conditions, or Parkinson’s disease), or for 2 weeks after stopping the MAOI drug. If you do not know if your prescription drug contains an MAOI, ask a doctor or pharmacist before taking this product.

Allergy Alert: Contains sodium metabisulfite, a sulfite that may cause allergic-type reactions.

Ask a doctor before use if you have

- chronic cough that lasts as occurs with smoking, asthma, or emphysema
- cough that occurs with too much phlegm (mucus)

Stop use and ask a doctor if

- side effects occur. You may report side effects to FDA at 1-800-FDA-1088.
- cough lasts more than 7 days, cough comes back, or occurs with fever, rash or headache that lasts. These could be signs of a serious condition.

If pregnant or breast-feeding,

ask a health professional before use.

Keep out of reach of children.

In case of overdose, get medical help or contact a Poison Control Center right away (1-800-222-1222).

Directions

- shake bottle well before use
- measure only with dosing cup provided
- do not use dosing cup with other products
- dose as follows or as directed by a doctor
- mL = milliliter

adults and children 12 years of age; and over | 10 mL every 12 hours,; not to exceed 20 mL in 24 hours
children 6 to under 12 years of age | 5 mL every 12 hours,; not to exceed 10 mL in 24 hours
children 4 to under 6 years of age | 2.5 mL every 12 hours,; not to exceed 5 mL in 24 hours
children under 4 years of age | do not use

Other information

- each 5 mL contains: sodium 5 mg
- store at 20° to 25°C (68° to 77°F)
- dosing cup provided

Inactive ingredients

artificial grape flavor, D&C Red #30 aluminum lake, FD&C Blue #1 aluminum lake, glycerin, high fructose corn syrup, methylparaben, polysorbate 80, polyvinyl acetate, povidone, propylparaben, purified water, sodium metabisulfite, sodium polystyrene sulfonate, sucrose, tartaric acid, tragacanth gum, triacetin, xanthan gum

Questions or comments?

1-800-289-8343

Package/Label Principal Display Panel

Hy•Vee®

Compare To Delsym® Active Ingredient

Cough DM

Dextromethorphan Polistirex Extended-Release Oral Suspension

Cough Suppressant

Grape-Flavored Liquid

12 HOUR RELIEF

Day or Night

ALCOHOL-FREE

Contains sodium metabisulfite, a sulfite that may cause allergic-type reactions

3 FL OZ (89 mL)